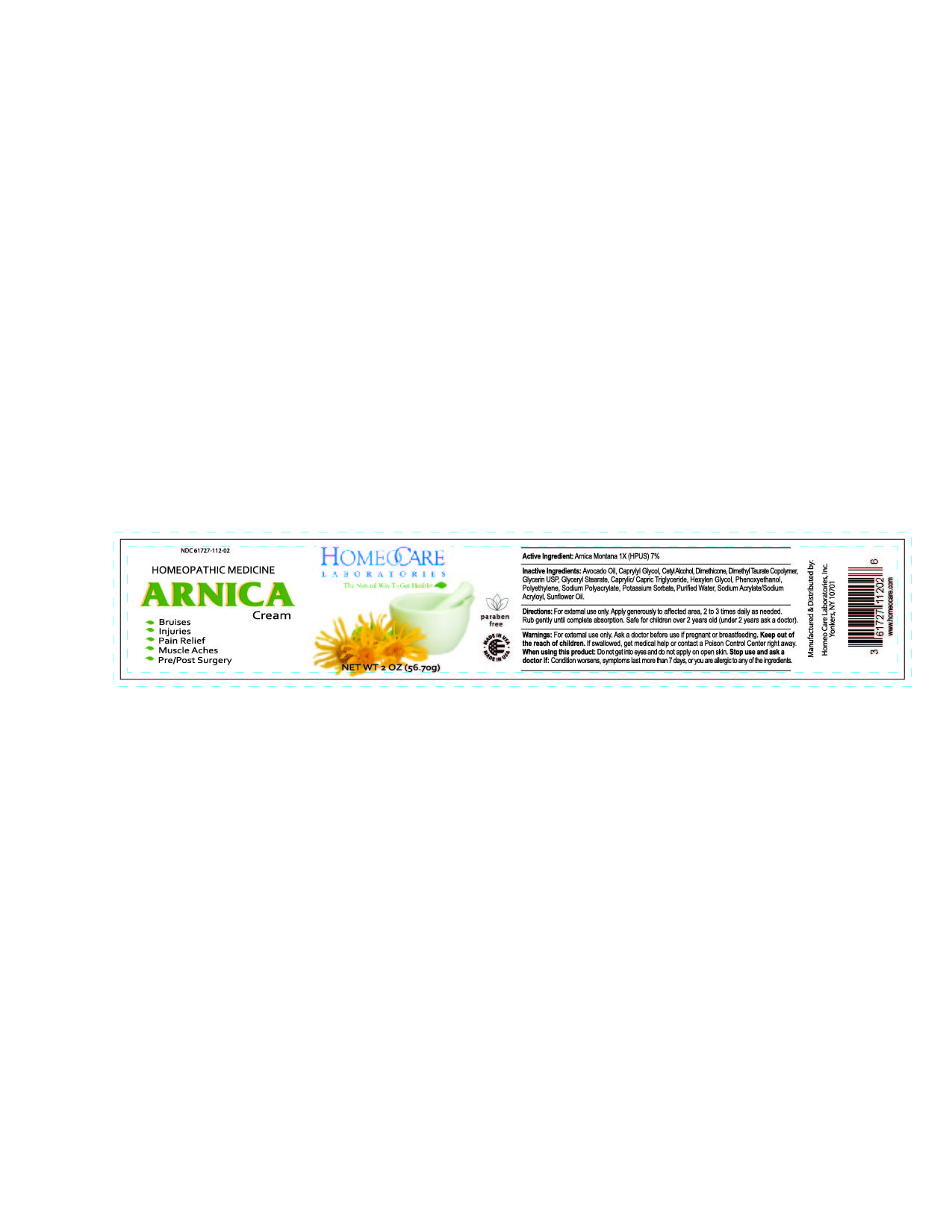 DRUG LABEL: Arnica Relief
NDC: 61727-112 | Form: CREAM
Manufacturer: Homeocare Laboratories
Category: homeopathic | Type: HUMAN OTC DRUG LABEL
Date: 20260112

ACTIVE INGREDIENTS: ARNICA MONTANA 1 [hp_X]/56.7 g
INACTIVE INGREDIENTS: AVOCADO OIL; CAPRYLYL GLYCOL; CETYL ALCOHOL; DIMETHICONE; SODIUM ACRYLATE/SODIUM ACRYLOYLDIMETHYLTAURATE COPOLYMER (4000000 MW); GLYCERIN; GLYCERYL MONOSTEARATE; TRICAPRIN; HEXYLENE GLYCOL; PHENOXYETHANOL; HIGH DENSITY POLYETHYLENE; SODIUM POLYACRYLATE (2500000 MW); POTASSIUM SORBATE; WATER; SODIUM ACRYLATE; SUNFLOWER OIL

Arnica Relief Cream

Active Ingredients:

Arnica Montana 1x (HPUS) 7%

Purpose:

As a topical aid for the relief of bruising, injuries, muscle aches, pain relief and pre-post surgically.

Keep out of the reach of children.

Indications for Usage:

As a topical aid for the relief of bruising, injuries, muscle aches, pain relief and pre-post surgically.

Warnings:

For external use only. Ask a doctor before use if pregnant or breastfeeding. Keep out of the reach of children.If swallowed, get medical help or contact a Poison Control Center right away.

Inactive Ingredients:

Avocado Oil, Caprylyl Glycol, Cetyl Alcohol, Dimethicone, Dimethyl Taurate Copolymer, Glycerin USP, Glyceryl Stearate, Caprylic/Capric Triglyceride, Hexylen Glycol, Phenoxyethanol, Polyethylene, Sodium Polyacrylate, Potassium Sorbate, Purified Water, Sodium Acrylate/Sodium Acryloyl, Sunflower Oil.

Dosage & Administration:

For external use only. Apply generously to affected area. 2 to 3 times daily or as needed. Rub gently until complete absorption. Safe for children over 2 years old (under 2 years ask a doctor).